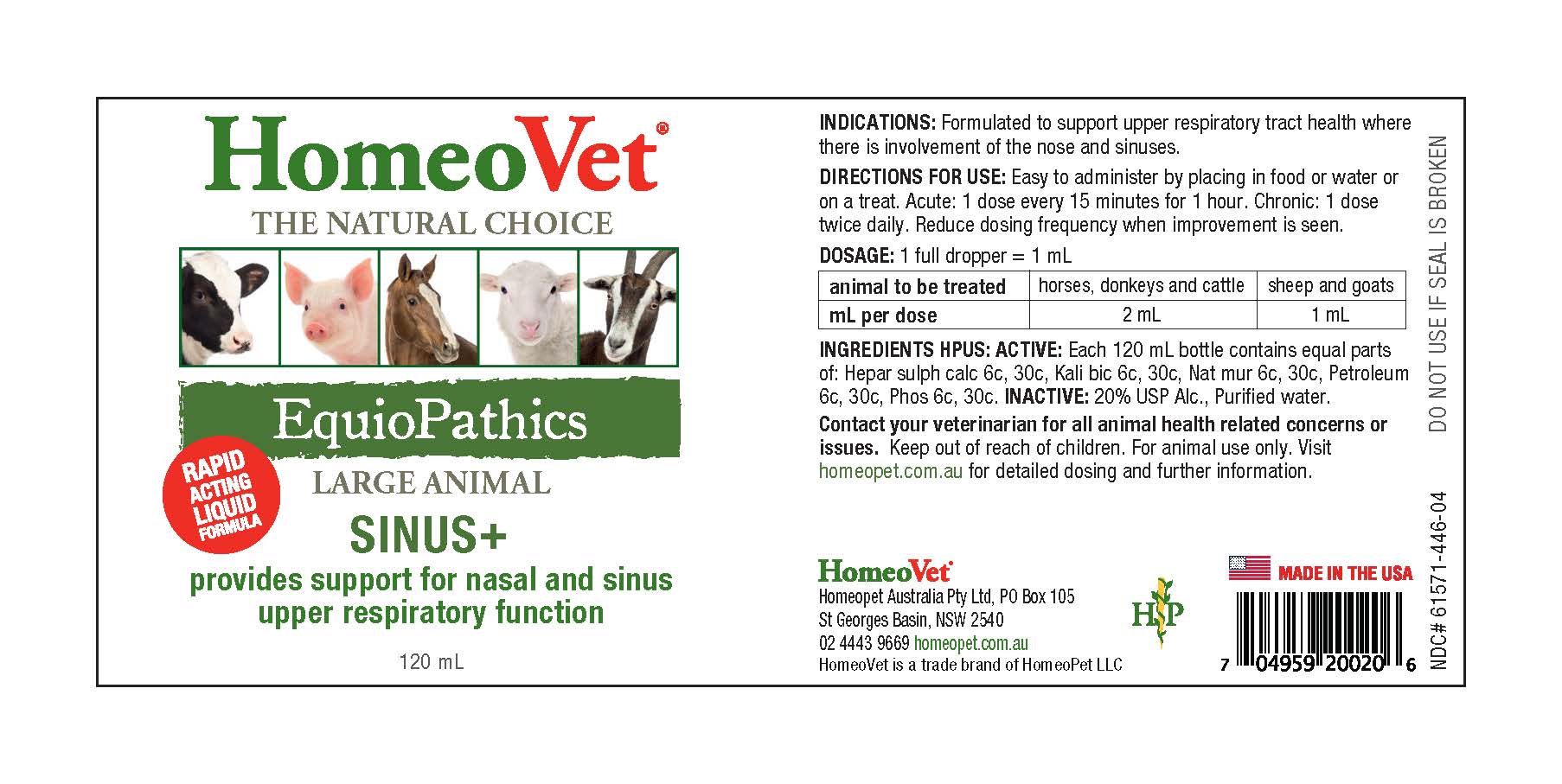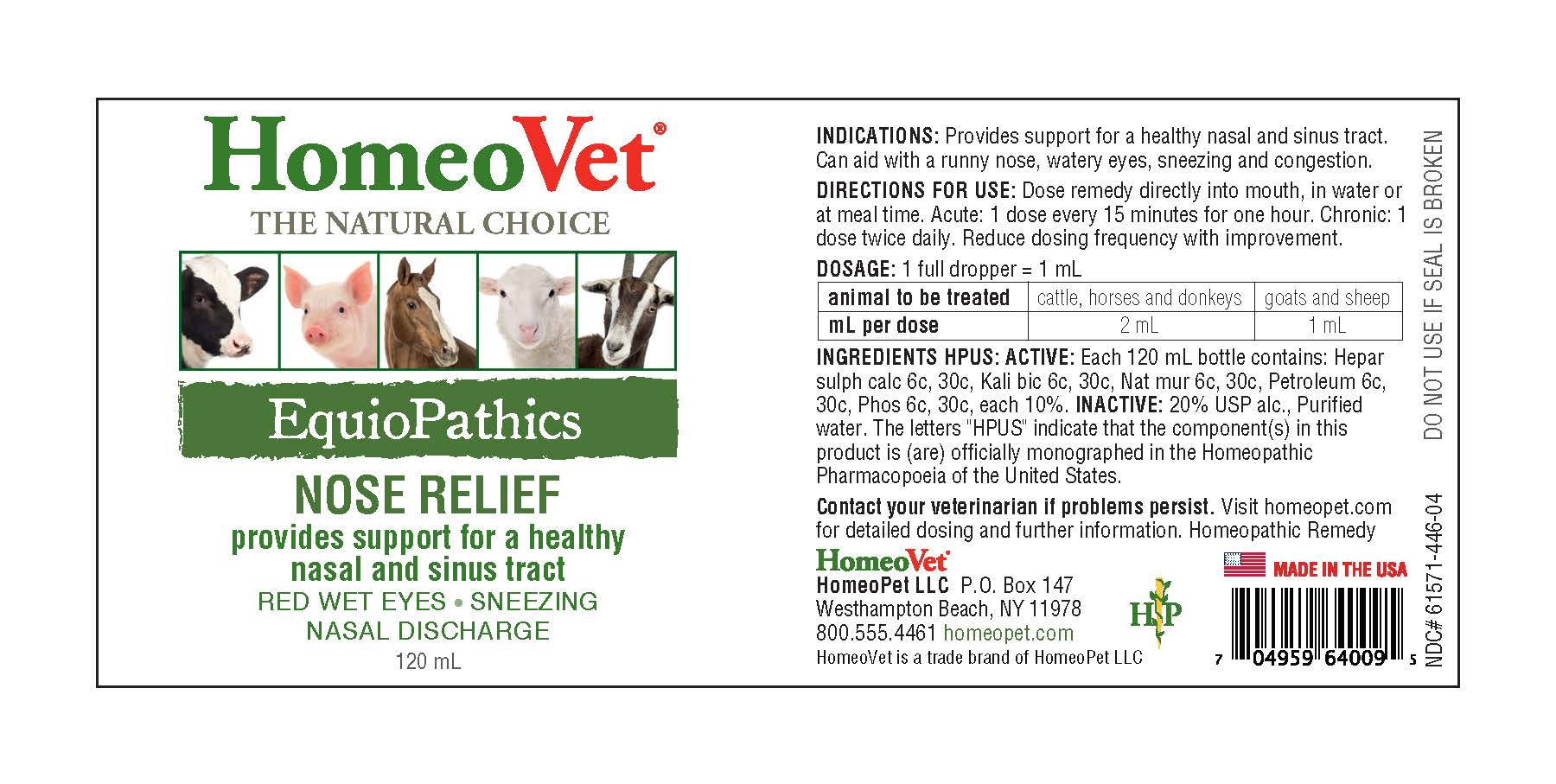 DRUG LABEL: EquioPathics Nose and Sinus
NDC: 61571-446 | Form: LIQUID
Manufacturer: HomeoPet, LLC
Category: homeopathic | Type: OTC ANIMAL DRUG LABEL
Date: 20251211

ACTIVE INGREDIENTS: CALCIUM SULFIDE 6 [hp_C]/120 mL; POTASSIUM DICHROMATE 6 [hp_C]/120 mL; SODIUM CHLORIDE 6 [hp_C]/120 mL; PHOSPHORUS 6 [hp_C]/120 mL; PETROLATUM 6 [hp_C]/120 mL
INACTIVE INGREDIENTS: ALCOHOL; WATER

EquioPathics Nose Relief

Provides support for a healthy nasal and sinus tract

RED WET EYES-SNEEZING-NASAL DISCHARGE

DIRECTIONS FOR USE AND DOSAGE

Dose remedy directly into mouth, in water or at meal time. Acute: 1 dose every 15 minutes for one hour. Chronic: 1 dose twice daily. Reduce dosing frequency with improvement.

animal to be treated | cattle, houses and donkeys | goats and sheep
mL per dose | 2 mL | 1 mL

INDICATIONS

Provides support for a healthy nasal and sinus tract. Can aid with a runny nose, watery eyes, sneezing and congestion.

Ingredients HPUS: ACTIVE

Hepar sulphuris calcareum 6c, 30c, Kali Bichromicum 6c, 30c, Natrum muriaticum 6c, 30c, Phosphorus 6c, 30c, Petroleum 6c, 30c

Inactive Ingredients

USP Alcohol, Purified water

ASK DOCTOR

Contact your veterinarian if problems persist.

Visit homeopet.com for detailed dosing and further information. Homeopathic Remedy.